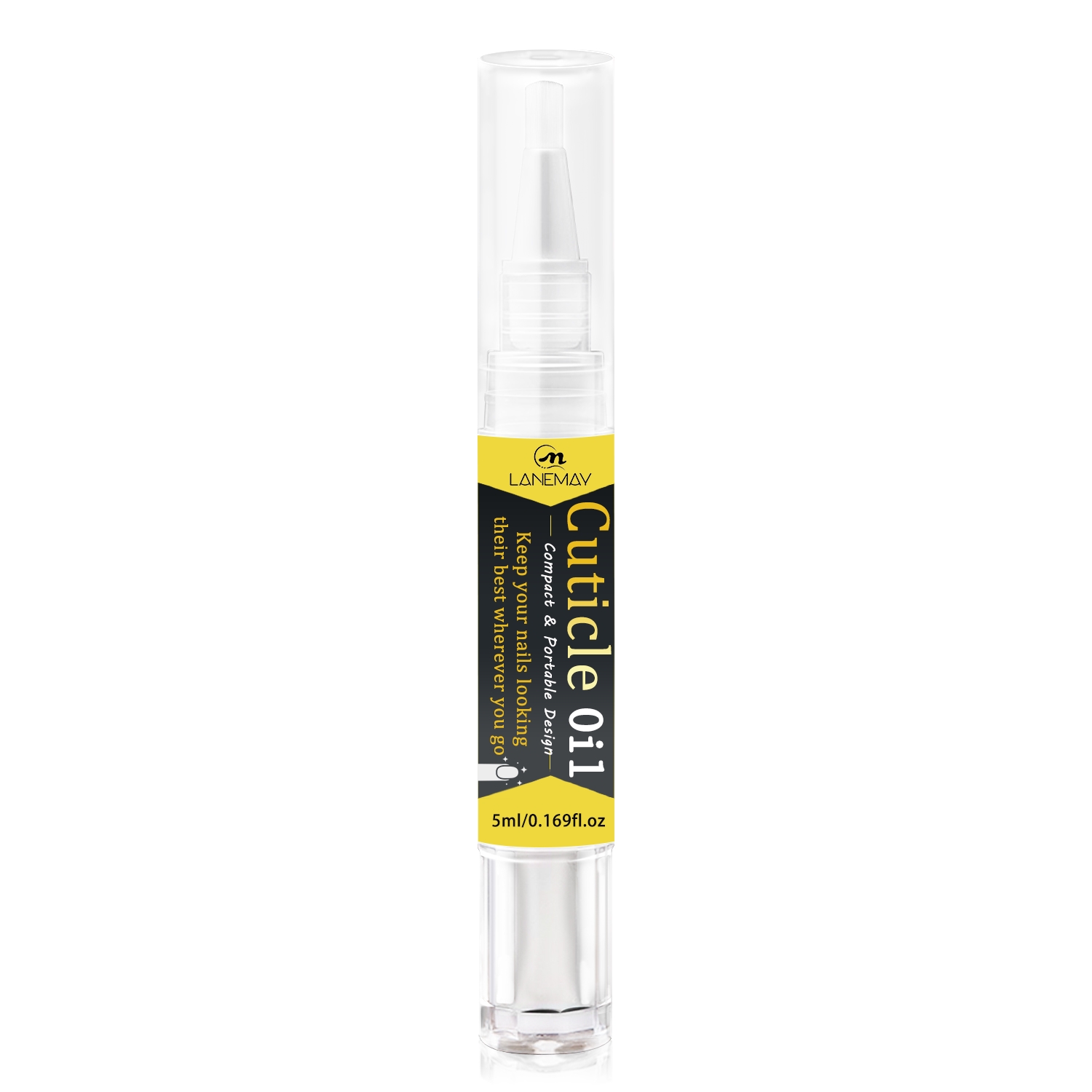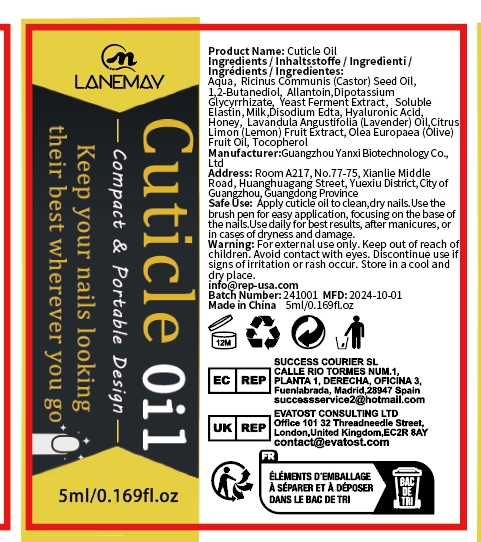 DRUG LABEL: Cuticle Oil
NDC: 84025-277 | Form: CREAM
Manufacturer: Guangzhou Yanxi Biotechnology Co., Ltd
Category: otc | Type: HUMAN OTC DRUG LABEL
Date: 20241203

ACTIVE INGREDIENTS: TOCOPHEROL 1 mg/5 mL; ALLANTOIN 2 mg/5 mL
INACTIVE INGREDIENTS: WATER

DOSAGE AND ADMINISTRATION

Apply cuticle oil ti clean,dry nails.Use the brush pen for easy application,focusing on the base of the nails.Use daily for best results,after manicures,or in cases of dryness and damage.

WARNINGS

Keep out of children

INACTIVE INGREDIENT

Aqua

INDICATIONS AND USAGE

For daily skin care

Keep out of children

PURPOSE

Keep nails looking best